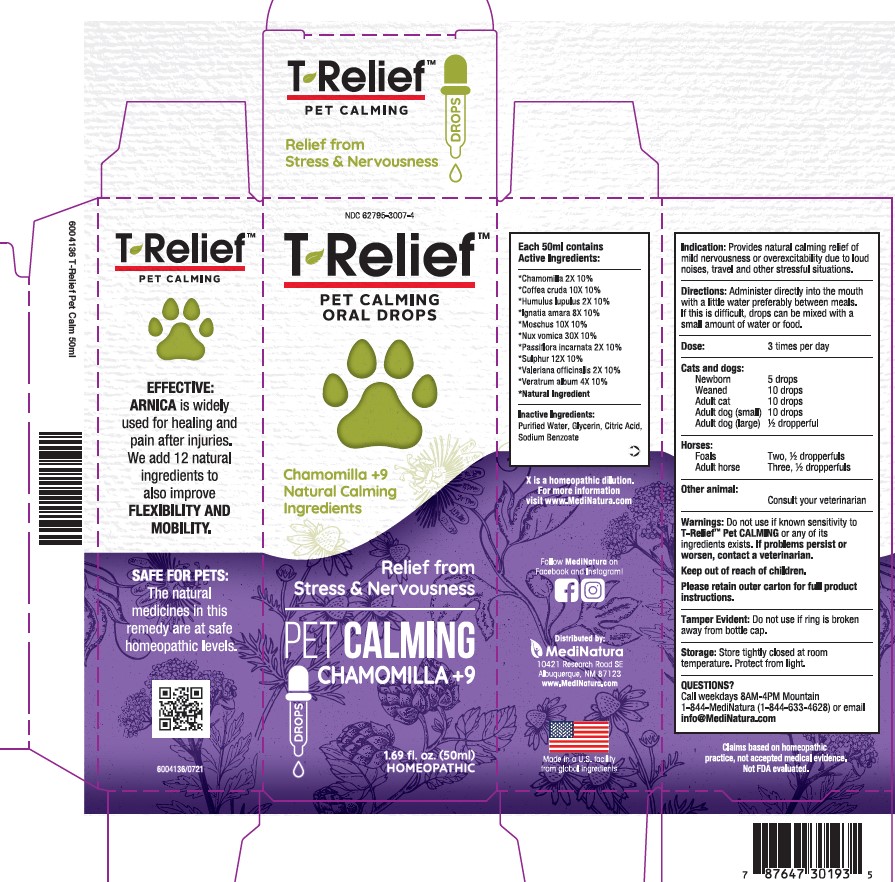 DRUG LABEL: T-Relief Pet Calming
NDC: 62795-3007 | Form: SOLUTION/ DROPS
Manufacturer: MediNatura New Mexico Inc
Category: homeopathic | Type: OTC ANIMAL DRUG LABEL
Date: 20230918

ACTIVE INGREDIENTS: MATRICARIA CHAMOMILLA 2 [hp_X]/50 mL; HOPS 2 [hp_X]/50 mL; PASSIFLORA INCARNATA FLOWERING TOP 2 [hp_X]/50 mL; VALERIAN 2 [hp_X]/50 mL; VERATRUM ALBUM ROOT 4 [hp_X]/50 mL; STRYCHNOS IGNATII SEED 8 [hp_X]/50 mL; ARABICA COFFEE BEAN 10 [hp_X]/50 mL; MOSCHUS MOSCHIFERUS MUSK SAC RESIN 10 [hp_X]/50 mL; SULFUR 12 [hp_X]/50 mL; STRYCHNOS NUX-VOMICA SEED 30 [hp_X]/50 mL
INACTIVE INGREDIENTS: WATER; GLYCERIN; CITRIC ACID ACETATE; Sodium Benzoate

T-Relief Pet Calming

Warnings:

Do not use if known sensitivity to T-Relief™ Pet CALMING
or any of its ingredients exists. If problems persist or worsen, contact a
veterinarian. Keep out of reach of children.

Indication:

Provides natural calming relief of mild nervousness or
overexcitability due to loud noises, travel and other stressful situations.

Directions

Directions: Administer directly into the mouth with a little water preferably
between meals. If this is difficult, drops can be mixed with a small amount
of water or food.–
Dose: 3 times per day – Cats & dogs: Newborn – 5 drops. Weaned – 10
drops. Adult cat – 10 drops. Adult dog (small) – 10 drops. Adult dog (large)
– ½ dropperful. Horses: Foals – Two, ½ dropperfuls. Adult horse – Three,
½ dropperfuls. Other animal: Consult your veterinarian.–

Inactive Ingredients:

Purified Water, Glycerin, Citric Acid, Sodium Benzoate

Keep out of reach of children

Purpose

Provides natural calming relief of mild nervousness or
overexcitability due to loud noises, travel and other stressful situations.

Active Ingredients

Each 50mL contains: *Chamomilla 2X 10%,
*Coffea cruda 10X 10%, *Humulus lupulus 2X 10%, *Ignatia amara 8X
10%, *Moschus 10X 10%, *Nux vomica 30X 10%, *Passiflora incarnata
2X 10%, *Sulphur 12X 10%, *Valeriana officinalis 2X 10%, *Veratrum
album 4X 10%